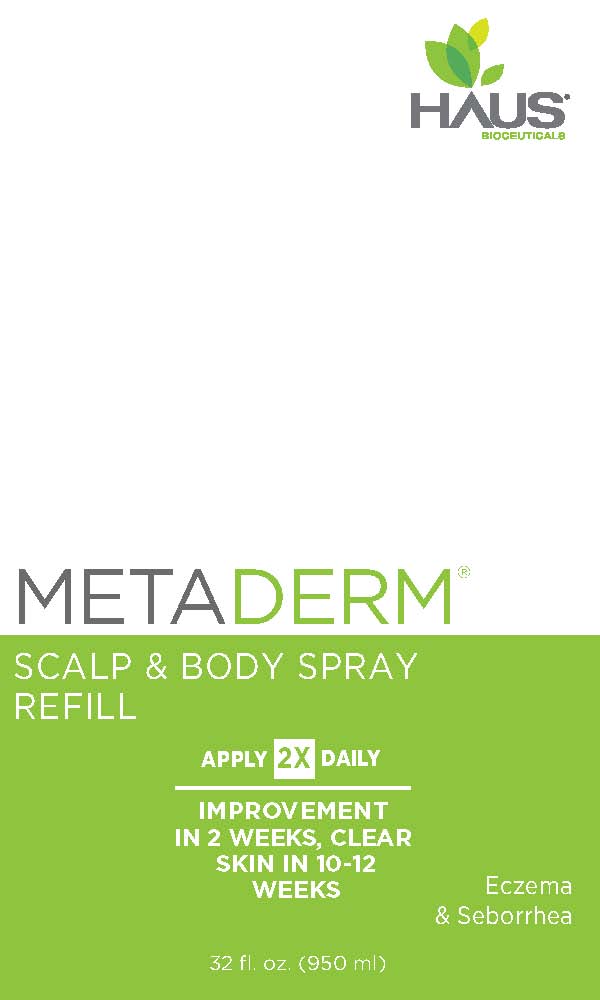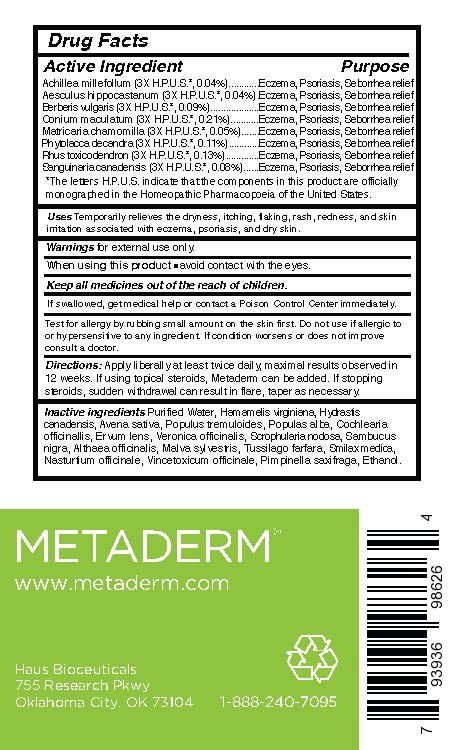 DRUG LABEL: Metaderm Scalp and Body
NDC: 58133-380 | Form: SPRAY
Manufacturer: Cosmetic Specialty Labs, Inc.
Category: homeopathic | Type: HUMAN OTC DRUG LABEL
Date: 20180816

ACTIVE INGREDIENTS: MATRICARIA CHAMOMILLA FLOWERING TOP OIL 5 [hp_M]/1 mL; SANGUINARIA CANADENSIS ROOT 8 [hp_M]/1 mL; ACHILLEA MILLEFOLIUM 4 [hp_M]/1 mL; BERBERIS VULGARIS FRUIT 9 [hp_M]/1 mL; CONIUM MACULATUM FRUIT 21 [hp_M]/1 mL; RHUS SPP. WHOLE 13 [hp_M]/1 mL; PHYTOLACCA OCTANDRA LEAF 11 [hp_M]/1 mL; AESCULUS HIPPOCASTANUM SEED OIL 4 [hp_M]/1 mL
INACTIVE INGREDIENTS: VERONICA OFFICINALIS LEAF; ALTHAEA OFFICINALIS LEAF; SCROPHULARIA NODOSA; WATER; 1-(3,5-BIS(TRIFLUOROMETHYL)PHENYL)ETHANOL; HAMAMELIS VIRGINIANA ROOT BARK/STEM BARK; TUSSILAGO FARFARA; HYDRASTIS CANADENSIS WHOLE; SAMBUCUS NIGRA FLOWER OIL; MALVA SYLVESTRIS LEAF; POPULUS TREMULOIDES LEAF; POPULUS ALBA LEAF; COCHLEARIA OFFICINALIS LEAF; SARSAPARILLA; NASTURTIUM OFFICINALE; VINCETOXICUM ATRATUM ROOT; PIMPINELLA SAXIFRAGA ROOT; LENS CULINARIS FRUIT; AVENA SATIVA LEAF

Metaderm Scalp and Body Spray

Active Ingredient

Achillea millefolium (3X H.P.U.S.*, 0.04%)
Aesculus hippocastanum (3X H.P.U.S.*, 0.04%)
Berberis vulgaris (3X H.P.U.S.*, 0.09%)
Conium maculatum (3X H.P.U.S.*, 0.21%)
Matricaria chamomilla (3X H.P.U.S.*, 0.05%)
Phytolacca decandra (3X H.P.U.S.*, 0.11%)
Rhus toxicodendron (3X H.P.U.S.*, 0.13%)
Sanguinaria canadensis (3X H.P.U.S.*, 0.08%)

Purpose

Psoriasis relief

*The letters H.P.U.S. indicate that the components in this product are officially monographed in the Homeopathic Pharmacopoeia of the United States.

Uses:

Temporarily relieves the dryness, itching, flaking, rash, redness, and skin
irritation associated with eczema, psoriasis, and dry skin.

Warnings:

for external use only

When using this product:

- Avoid contact with eyes.
- If swallowed, get medical help or contact a Poison Control Center immediately.
- Test for allergy by rubbing small amount on skin first.
- Do not use if allergic to or hypersensitive to any ingredient.
- If condition worsens or does not improve consult a doctor.

Keep all medicines out of reach of children.

Directions:

Apply liberally at least twice daily, maximal results observed in
12 weeks. If using topical steroids, Metaderm can be added. If stopping
steroids, sudden withdrawal can result in flare, taper as necessary.

Other ingredients:

Purified Water, Hamamelis virginiana, Hydrastis
canadensis, Avena sativa, Populus tremuloides, Populas alba, Cochlearia
officinallis, Ervum lens, Veronica officinalis, Scrophularia nodosa, Sambucus
nigra, Althaea officinalis, Malva sylvestris, Tussilago farfara, Smilax medica,
Nasturtium officinale, Vincetoxicum officinale, Pimpinella saxifraga, Ethanol.